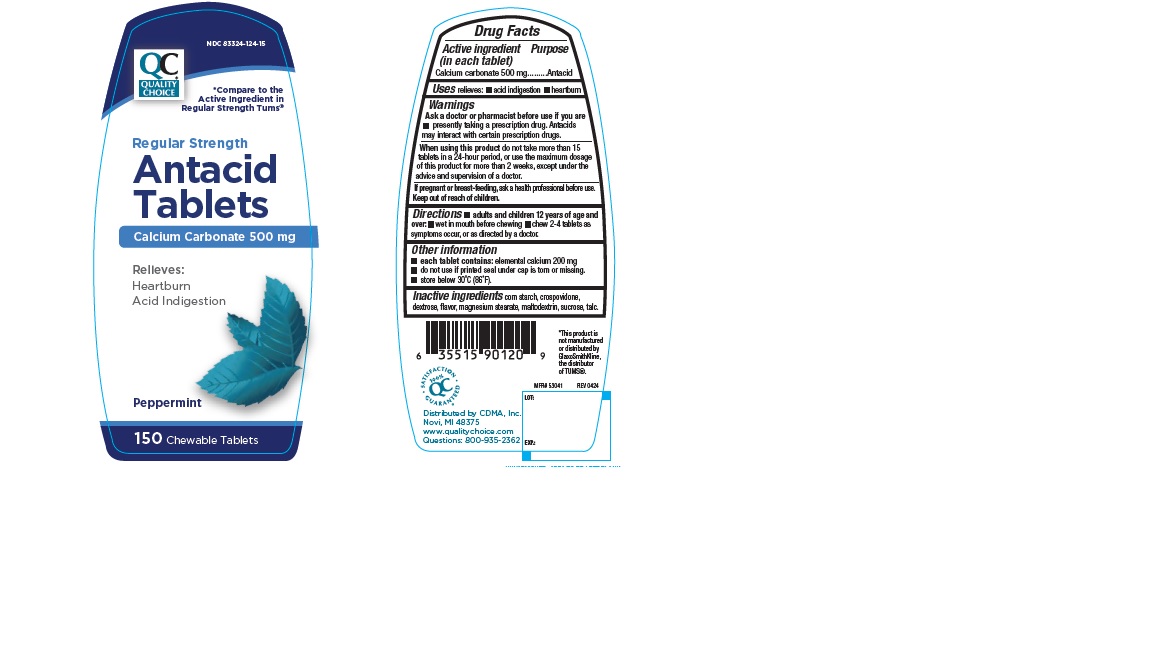 DRUG LABEL: QCH Regular Strength Antacid Peppermint 113
NDC: 83324-124 | Form: TABLET, CHEWABLE
Manufacturer: Chain Drug Marketing Association Inc.
Category: otc | Type: Human OTC Drug Label
Date: 20240628

ACTIVE INGREDIENTS: CALCIUM CARBONATE 500 mg/1 1
INACTIVE INGREDIENTS: STARCH, CORN; DEXTROSE, UNSPECIFIED FORM; MAGNESIUM STEARATE; MALTODEXTRIN; SUCROSE; TALC; CROSPOVIDONE, UNSPECIFIED

QCH Regular Strength Antacid peppermint Chewable 113

ACTIVE INGREDIENT (in each tablet)

Calcium carbonate 500 mg

PURPOSE

Antacid

USES

relieves:

- acid indigestion
- heartburn

WARNINGS

.

ASK A DOCTOR OR PHARMACIST BEFORE USE IF YOU ARE

- presently taking a prescription drug. Antacids may interact with certain prescription drugs.

WHEN USING THIS PRODUCT

do not take more than 15 tablets in a 24-hour period, or use the maximum dosage of this product for more than 2 weeks, except under the advice and supervision of a doctor.

IF PREGNANT OR BREAST FEEDING,

ask a health professional before use.

KEEP OUT OF REACH OF CHILDREN

.

DIRECTIONS

- adults and children 12 years of age and over:
- Wet in mouth before chewing
- chew 2-4 tablets as symptoms occur, or as directed by a doctor.

OTHER INFORMATION

- each tablet contains: elemental calcium 200 mg
- do not use if printed seal under the cap is torn or missing.
- store below 30oC (86o F).

INACTIVE INGREDIENTS

corn starch, crospovidone, dextrose, flavor, magnesium stearate, maltodextrin, sucrose, talc.

PRINCIPAL DISPLAY PANEL

NDC83324-124-15

QUALITY CHOICE

*Compare to the active ingredient in Regular Strength Tums®

Regular Strength Antacid Tablets
Calcium Carbonate 500 mg

Relieves:

Heartburn

Acid Indigestion

Peppermint

150 chewable tablets